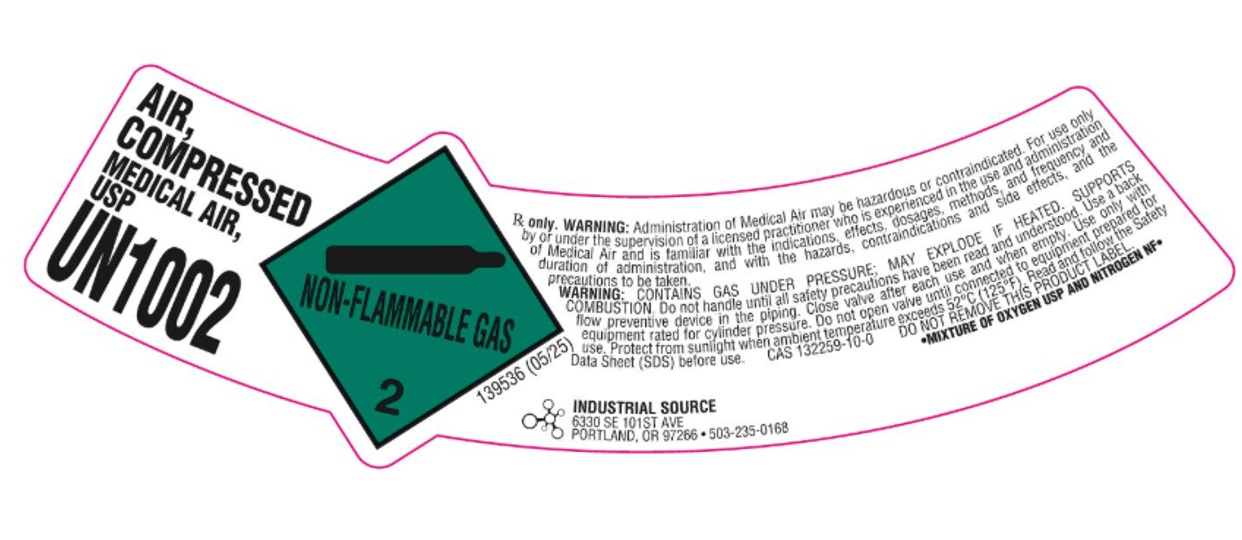 DRUG LABEL: Air
NDC: 64169-003 | Form: GAS
Manufacturer: EUGENE WELDERS SUPPLY CO
Category: prescription | Type: HUMAN PRESCRIPTION DRUG LABEL
Date: 20251029

ACTIVE INGREDIENTS: OXYGEN 210 mL/1 L
INACTIVE INGREDIENTS: NITROGEN 790 mL/1 L

Air Label

PACKAGE LABEL

AIR, COMPRESSED

MEDICAL AIR, USP

UN1002

Rx only. WARNING: Administration of Medical Air may be hazardous or contraindicated. For use only by or under the supervision of a licensed practitioner who is experienced in the use and administration of Medical Air and is familiar with the indications, effects, dosages, methods, and frequency and duration of administration, and with the hazards, contraindications and side effects, and the precautions to be taken.

WARNING: CONTAINS GAS UNDER PRESSURE; MAY EXPLODE IF HEATED. SUPPORTS COMBUSTION. Do not handle until all safety precautions have been read and understood. Use a back flow preventive device in the piping. Close valve after each use and when empty. Use only with equipment rated for cylinder pressure. Do not open valve until connected to equipment prepared for use. Protect from sunlight when ambient temperature exceeds 52 C (125 F). Read and follow the Safety Data Sheet (SDS) before use.

CAS 132259-10-0 DO NOT REMOVE THIS PRODUCT LABEL

*MIXTURE OF OXYGEN USP AND NITROGEN NF*

INDUSTRIAL SOUCE

6330 SE 101ST AVE

PORTLAND, OR 97266 503-235-0168